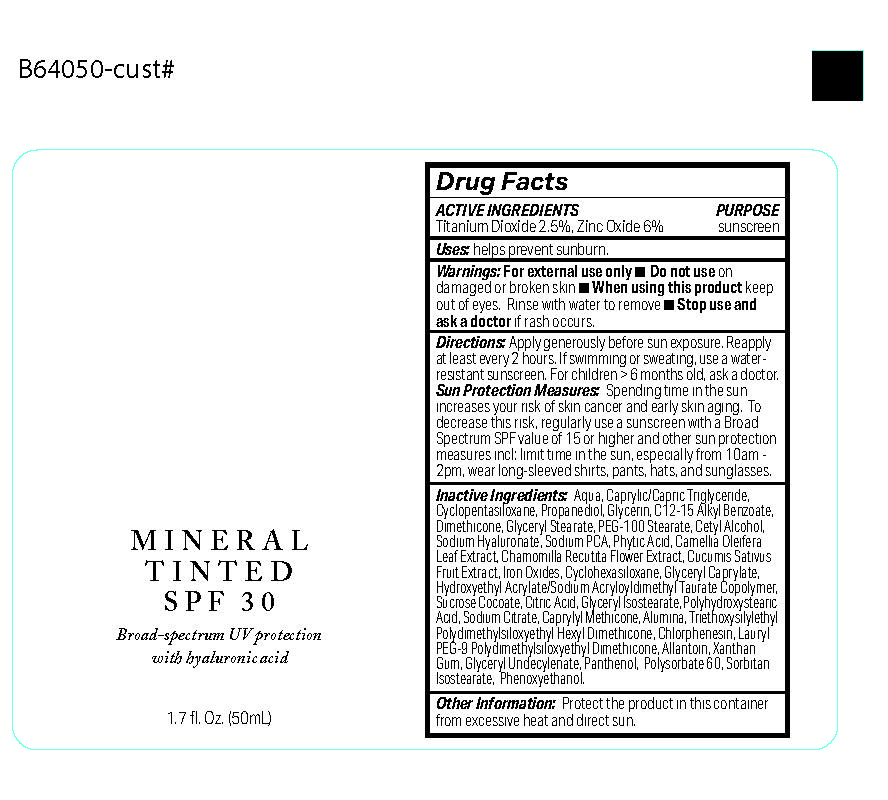 DRUG LABEL: MINERAL TINTED SPF 30
NDC: 70712-104 | Form: LOTION
Manufacturer: BOTANICAL SCIENCE, INC.
Category: otc | Type: HUMAN OTC DRUG LABEL
Date: 20250304

ACTIVE INGREDIENTS: TITANIUM DIOXIDE 2.5 g/100 mL; ZINC OXIDE 6 g/100 mL
INACTIVE INGREDIENTS: CYCLOPENTASILOXANE; CHAMOMILE; SUCROSE COCOATE; POLYSORBATE 60; LAURYL PEG-9 POLYDIMETHYLSILOXYETHYL DIMETHICONE; PHYTIC ACID; SODIUM CITRATE, UNSPECIFIED FORM; SORBITAN ISOSTEARATE; DIMETHICONE; ALUMINA; POLYHYDROXYSTEARIC ACID (2300 MW); IRON OXIDES; CUCUMIS SATIVUS (CUCUMBER) FRUIT; GLYCERYL CAPRYLATE; GLYCERYL STEARATE; GLYCERYL ISOSTEARATE; CYCLOHEXASILOXANE; CAPRYLIC/CAPRIC TRIGLYCERIDE; TRIETHOXYSILYLETHYL POLYDIMETHYLSILOXYETHYL HEXYL DIMETHICONE; ALLANTOIN; PANTHENOL; SODIUM HYALURONATE; SODIUM PCA; CAMELLIA OLEIFERA LEAF; ALKYL (C12-15) BENZOATE; CETYL ALCOHOL; WATER; PEG-100 STEARATE; XANTHAN GUM; PHENOXYETHANOL; GLYCERIN; HYDROXYETHYL ACRYLATE/SODIUM ACRYLOYLDIMETHYL TAURATE COPOLYMER (45000 MPA.S AT 1%); CITRIC ACID; PROPANEDIOL; CAPRYLYL METHICONE; CHLORPHENESIN

BOTANICAL SCIENCE - MINERAL TINTED SPF 30 (70712-104)

ACTIVE INGREDIENTS

TITANIUM DIOXIDE 2.5%

ZINC OXIDE 6.0%

PURPOSE

SUNSCREEN

USES

HELPS PREVENT SUNBURN.

WARNINGS

FOR EXTERNAL USE ONLY.

- Do not use on damaged or broken skin.
- When using this product keep out of eyes. Rinse with water to remove.
- Stop use and ask a doctor if rash occurs.

DIRECTIONS

APPLY GENEROUSLY 15 MINUTES BEFORE SUN EXPOSURE. REAPPLY AT LEAST EVERY 2 HOURS. IF SWIMMING OR SWEATING, USE A WATER-RESISTANT SUNSCREEN. FOR CHILDREN UNDER 6 MONTHS OF AGE: ASK A DOCTOR.

SUN PROTECTION MEASURES

SPENDING TIME IN THE SUN INCREASES YOUR RISK OF SKIN CANCER AND EARLY SKIN AGING. TO DECREASE THIS RISK, REGULARLY USE A SUNSCREEN WITH A BROAD SPECTRUM SPF VALUE OF 15 OR HIGHER AND OTHER SUN PROTECTION MEASURES INCLUDING: LIMIT TIME IN THE SUN, ESPECIALLY FROM 10AM - 2PM, WEAR LONG-SLEEVED SHIRTS, PANTS, HATS, AND SUNGLASSES.

Keep out of reach of children.

INACTIVE INGREDIENTS

AQUA, CAPRYLIC/CAPRIC TRIGLYCERIDE, CYCLOPENTASILOXANE, PROPANEDIOL, GLYCERIN, C12-15 ALKYL BENZOATE, DIMETHICONE, GLYCERYL STEARATE, PEG-100 STEARATE, CETYL ALCOHOL, SODIUM HYALURONATE, SODIUM PCA, PHYTIC ACID, CAMELLIA OLEIFERA LEAF EXTRACT, CHAMOMILLA RECUTITA FLOWER EXTRACT, CUCUMIS SATIVUS FRUIT EXTRACT, IRON OXIDES, CYCLOHEXASILOXANE, GLYCERYL CAPRYLATE, HYDROXYETHYL ACRYLATE/SODIUM ACRYLOYLDIMETHYL TAURATE COPOLYMER, SUCROSE COCOATE, CITRIC ACID, GLYCERYL ISOSTEARATE, POLYHYDROXYSTEARIC ACID, SODIUM CITRATE, CAPRYLYL METHICONE, ALUMINA, TRIETHOXYSILYLETHYL POLYDIMETHYLSILOXYETHYL HEXYL DIMETHICONE, CHLORPHENESIN, LAURYL PEG-9 POLYDIMETHYLSILOXYETHYL DIMETHICONE, ALLANTOIN, XANTHAN GUM, GLYCERYL UNDECYLENATE, PANTHENOL, POLYSORBATE 60, SORBITAN ISOSTEARATE, PHENOXYETHANOL.